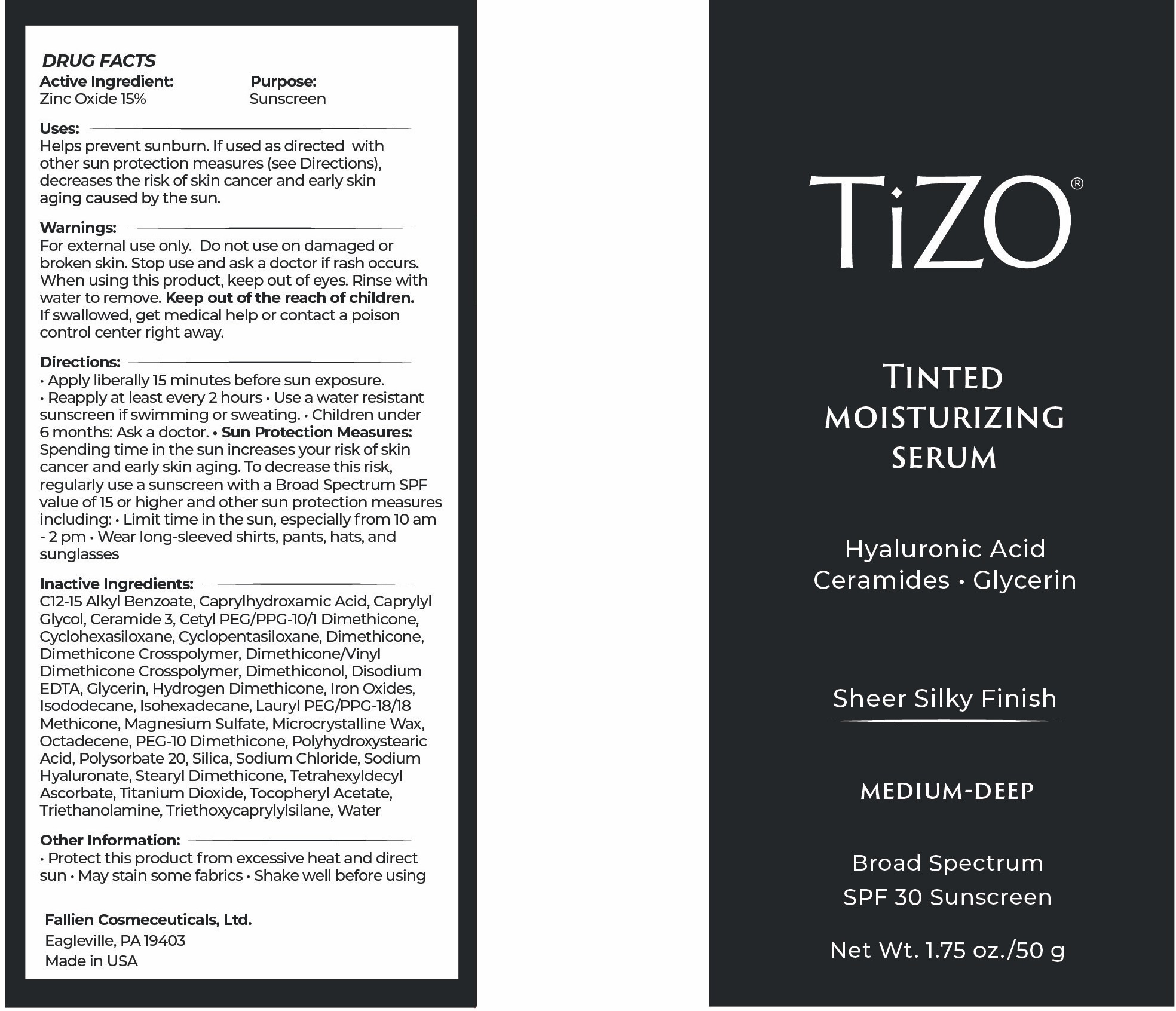 DRUG LABEL: TiZO Tinted Moisturizing Serum - Medium-Deep
NDC: 58892-134 | Form: CREAM
Manufacturer: Fallien Cosmeceuticals, Ltd.
Category: otc | Type: HUMAN OTC DRUG LABEL
Date: 20251216

ACTIVE INGREDIENTS: ZINC OXIDE 150 mg/1 g
INACTIVE INGREDIENTS: CI 77499; CAPRYLHYDROXAMIC ACID; CAPRYLYL GLYCOL; CERAMIDE 3; CETYL PEG/PPG-10/1 DIMETHICONE (HLB 4); EDETATE DISODIUM ANHYDROUS; C12-15 ALKYL BENZOATE; HYDROGEN DIMETHICONE (20 CST); ISOHEXADECANE; PEG-10 DIMETHICONE (600 CST); POLYHYDROXYSTEARIC ACID (2300 MW); ALPHA-TOCOPHEROL ACETATE; DIMETHICONE/VINYL DIMETHICONE CROSSPOLYMER (SOFT PARTICLE); DIMETHICONOL (2000 CST); POLYSORBATE 20; STEARYL DIMETHICONE (400 MPA.S AT 50C); SILICON DIOXIDE; MICROCRYSTALLINE WAX; SODIUM CHLORIDE; LAURYL PEG/PPG-18/18 METHICONE; MAGNESIUM SULFATE; SODIUM HYALURONATE; TITANIUM DIOXIDE; TRIETHANOLAMINE; WATER; OCTADECENE; TETRAHEXYLDECYL ASCORBATE; CYCLOPENTASILOXANE; GLYCERIN; DIMETHICONE CROSSPOLYMER; DIMETHICONE; TRIETHOXYCAPRYLYLSILANE; CI 77491; CYCLOHEXASILOXANE; ISODODECANE; CI 77492

Active Inhgredients:

Zinc Oxide 15%

Purpose:

Sunscreen

Uses:

Helps prevents sunburn. If used as directed with other sun protection measures (see Directions), decreases the risk of skin cancer and early skin aging caused by the sun.

Warnings:

For external use only. Do not use on damaged or broken skin. Stop use and ask a doctor if rash occurs. When using this product, keep out of eyes. Rinse with water to remove. Keep out of the reach of children. If swallowed, get medical help or contact a poison control center right away.

Directions:

Apply liberally 15 minutes before sun exposure. Use a water resistant product if swimming or sweating. Reapply At least every 2 hours. Children under 6 months: Ask a doctor. Sun Protection Measures: Spending time in the sun increases your risk of skin cancer and early skin aging. To decrease this risk, regularly use a sunscreen with a Broad Spectrum SPF value of 15 or higher and other sun protection measures including: Limit time in the sun, especially from 10 a.m. - 2 p.m. Wear long-sleeved shirts, pants, hats, and sunglasses

Inactive Ingredients:

C12-15 Alkyl Benzoate, Caprylhydroxamic Acid, Caprylyl Glycol, Ceramide 3, Cetyl PEG/PPG-10/1 Dimethicone, Cyclohexasiloxane, Cyclopentasiloxane, Dimethicone, Dimethicone Crosspolymer, Dimethicone/Vinyl Dimethicone Crosspolymer, Dimethiconol, Disodium EDTA, Glycerin, Hydrogen Dimethicone, Iron Oxides, Isododecane, Isohexadecane, Lauryl PEG/PPG-18/18 Methicone, Magnesium Sulfate, Microcrystalline Wax, Octadecene, PEG-10 Dimethicone, Polyhydroxystearic Acid, Polysorbate 20, Silica, Sodium Chloride, Sodium Hyaluronate, Stearyl Dimethicone, Tetrahexyldecyl Ascorbate, Titanium Dioxide,
Tocopheryl Acetate, Triethanolamine, Triethoxycaprylylsilane, Water

Other Information:

Protect this product from excessive heat and direct sun. May stain some fabrics. Shake well before using.

Warnings:

Keep out of the reach of children.